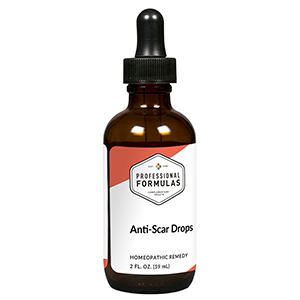 DRUG LABEL: Anti-Scar Drops
NDC: 63083-2084 | Form: LIQUID
Manufacturer: Professional Complementary Health Formulas
Category: homeopathic | Type: HUMAN OTC DRUG LABEL
Date: 20190815

ACTIVE INGREDIENTS: THUJA OCCIDENTALIS LEAF 3 [hp_X]/59 mL; ACONITUM NAPELLUS WHOLE 6 [hp_X]/59 mL; POTASSIUM ALUM 6 [hp_X]/59 mL; SILICON DIOXIDE 6 [hp_X]/59 mL; ANHYDROUS DIBASIC CALCIUM PHOSPHATE 6 [hp_X]/59 mL; ALLYLTHIOUREA 6 [hp_X]/59 mL; NITRIC ACID 8 [hp_X]/59 mL; GRAPHITE 12 [hp_X]/59 mL; LACTOSE, X-RAY EXPOSED (1000 RAD) 60 [hp_X]/59 mL; ARNICA MONTANA WHOLE 100 [hp_X]/59 mL
INACTIVE INGREDIENTS: ALCOHOL; WATER

C84

ACTIVE INGREDIENTS

Thuja occidentalis 3X, 6X, 12X, 24X, 30X
Aconitum napellus 6X
Alumen 6X
Silicea 6X
Calcarea phosphorica 6X, 12X
Thiosinaminum 6X, 12X
Nitricum acidum 8X
Graphites 12X
X-ray 60X
Arnica montana 100X

QUESTIONS

Professional Formulas

PO Box 2034 Lake Oswego, OR 97035

INDICATIONS

For the temporary relief of painful, sensitive, or itchy skin resulting from injury.*

PURPOSE

*Claims based on traditional homeopathic practice, not accepted medical evidence. Not FDA evaluated.

WARNINGS

In case of overdose, get medical help or contact a poison control center right away.

Keep out of the reach of children.

PREGNANCY OR BREAST FEEDING

If pregnant or breastfeeding, ask a healthcare professional before use.

DIRECTIONS

Place drops under tongue 30 minutes before/after meals. Adults and children 12 years and over: Take 10 drops up to 3 times per day. Consult a physician for use in children under 12 years of age.

OTHER INFORMATION

Tamper resistant. If seal is broken, do not use. After opening, close container tightly and store at room temperature away from heat.

INACTIVE INGREDIENTS

20% ethanol, purified water.

LABEL

Est 1985

Professional Formulas

Complementary Health

Anti-Scar Drops

Homeopathic Remedy

2 FL. OZ. (59 mL)